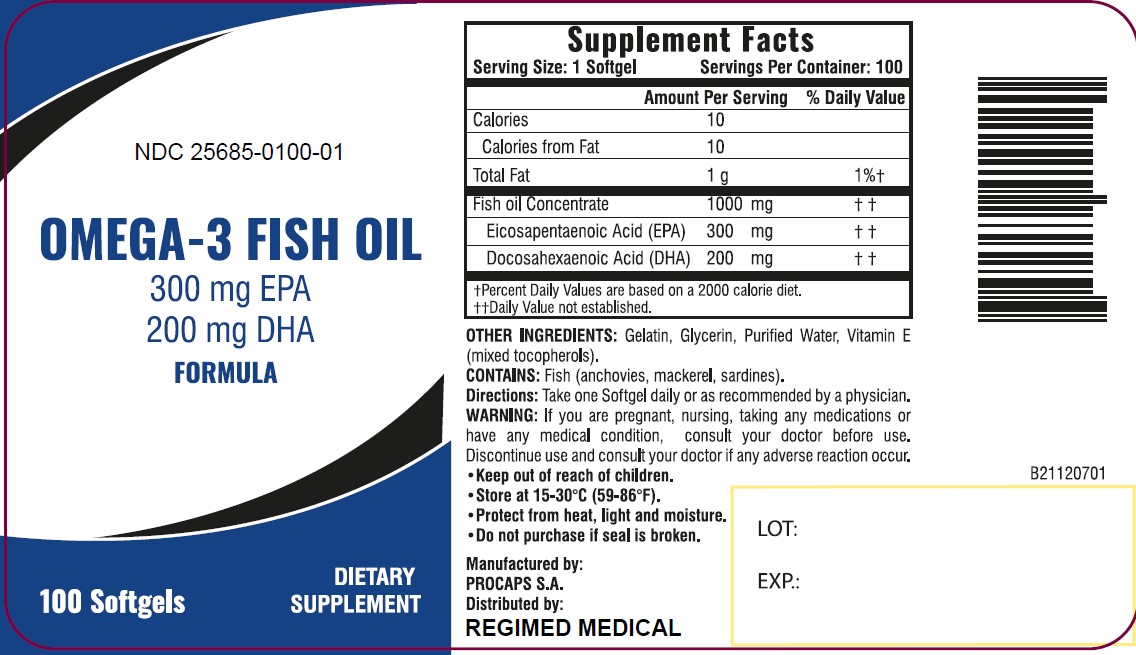 DRUG LABEL: Omega3 Fish Oil
NDC: 25685-100 | Form: CAPSULE, GELATIN COATED
Manufacturer: Regimed Medical
Category: other | Type: Dietary Supplement
Date: 20211216

ACTIVE INGREDIENTS: FISH OIL 1000 mg/1 1
INACTIVE INGREDIENTS: GELATIN; GLYCERIN; WATER; TOCOPHEROL

Omega 3 Fish Oil

PACKAGE LABEL

NDC 25685-0100-01

OMEGA-3 FISH OIL

300 mg EPA

200 mg DHA

FORMULA

100 Softgels

DIETARY SUPPLEMENT

Supplement Facts
Serving Size: 1 Softgel | Servings Per Container: 100
 | Amount Per Serving | % Daily Value
Calories | 10
Calories from Fat | 10
Total Fat | 1 g | 1% †
Fish oil Concentrate | 1000 mg | † †
Elcosapentaenoic Acid (EPA) | 300 mg | † †
Docosahexaenoic Acid (DHA) | 200 mg | † †
† Percent Daily Values are based on a 2000 calorie diet.
†† Daily Value not established.

OTHER INGREDIENTS: Gelatin, Glycerin, Purified Water, Vitamin E (mixed tocopherols)

CONTAINS: Fish (anchovies, mackerel, sardines).

Directions: Take one Softgel daily or as recommended by a physician.

WARNING: If you are pregnant, nursing, taking any medications or have any medical condition, consult your doctor before use. Discontinue use and consult your doctor if any adverse reaction occur.

- Keep out of reach of children.
- Store at 15-30°C (59-86°F).
- Protect from heat, light and moisture.
- Do not purchase if seal is broken.

Manufactured by:

PROCAPS S.A.

Distributed by:

REGIMED MEDICAL

STATEMENT OF IDENTITY

Omega-3 Fish Oil